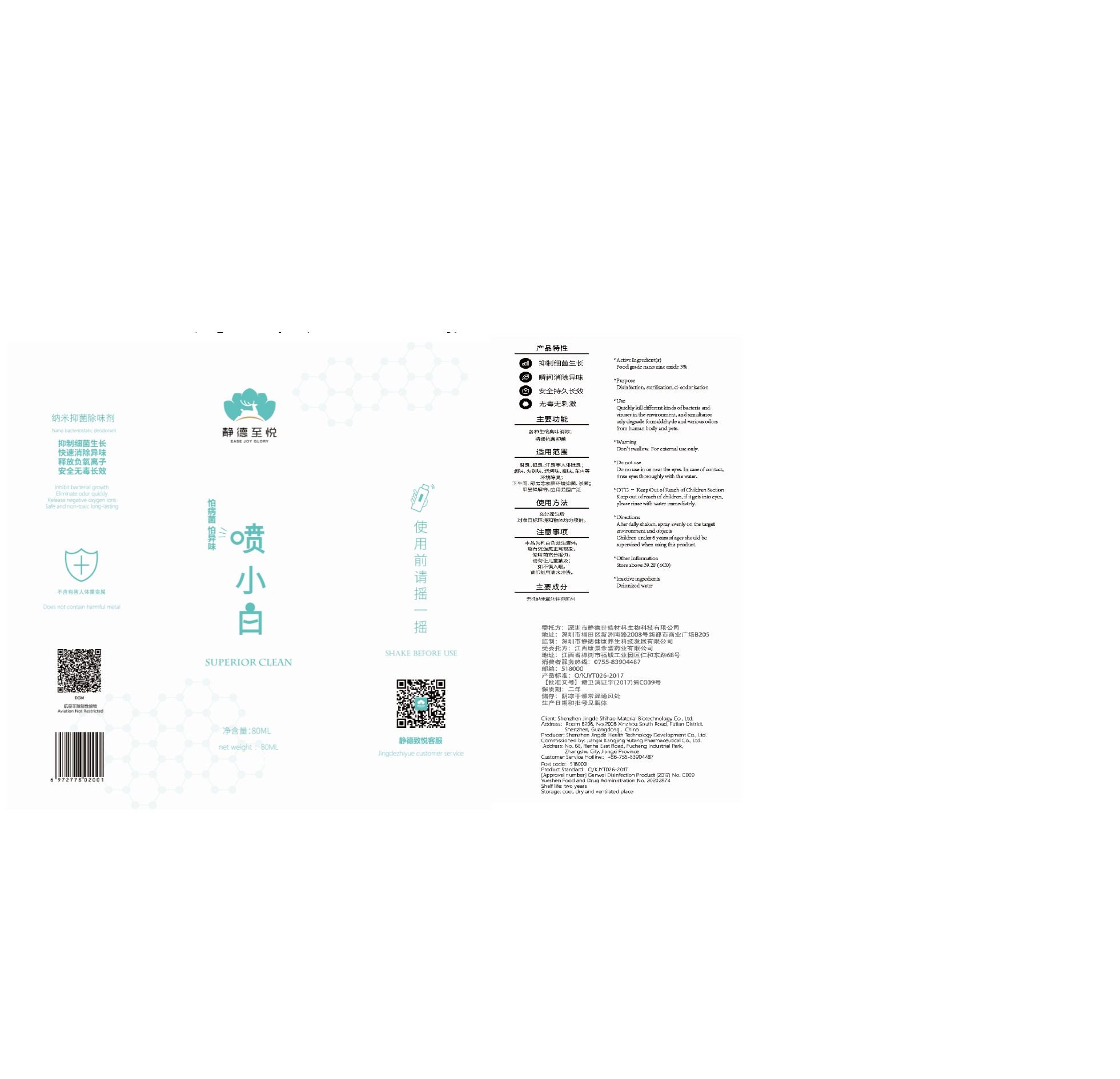 DRUG LABEL: Namo bacteriostatic deodorant
NDC: 74250-001 | Form: SPRAY
Manufacturer: Shenzhen Jingde Shihao Material Biotechnology Co.,Ltd.
Category: otc | Type: HUMAN OTC DRUG LABEL
Date: 20200329

ACTIVE INGREDIENTS: ZINC OXIDE 3 g/100 mL
INACTIVE INGREDIENTS: WATER

Active Ingredient(s)

Food grade nano zinc oxide 3%

Purpose

Disinfection, sterilization, deodorization

Use

Quickly kill different kinds of bacteria and viruses in the environment, and simultaneously degrade formaldehyde and various odors from human body and pets

Warnings

Don't swallow. For external use only.

Do not use

- o no use in or near the eyes. In case of contact, rinse eyes thoroughly with the water.

When using this product keep out of eyes, ears, and mouth. In case of contact with eyes, rinse eyes thoroughly with water.
Stop use and ask a doctor if irritation or rash occurs. These may be signs of a serious condition.
Keep out of reach of children. If swallowed, get medical help or contact a Poison Control Center right away.

Stop use and ask a doctor if irritation or rash occurs. These may be signs of a serious condition.

Keep out of reach of children, if it gets into eyes, please rinse with water immediately.

Directions

- After fully shaken, spray evenly on the target environment and objects
  Children under 6 years of ages should be supervised when using this product.

Other information

- Store above 39.2F (4C0)

Inactive ingredients

water